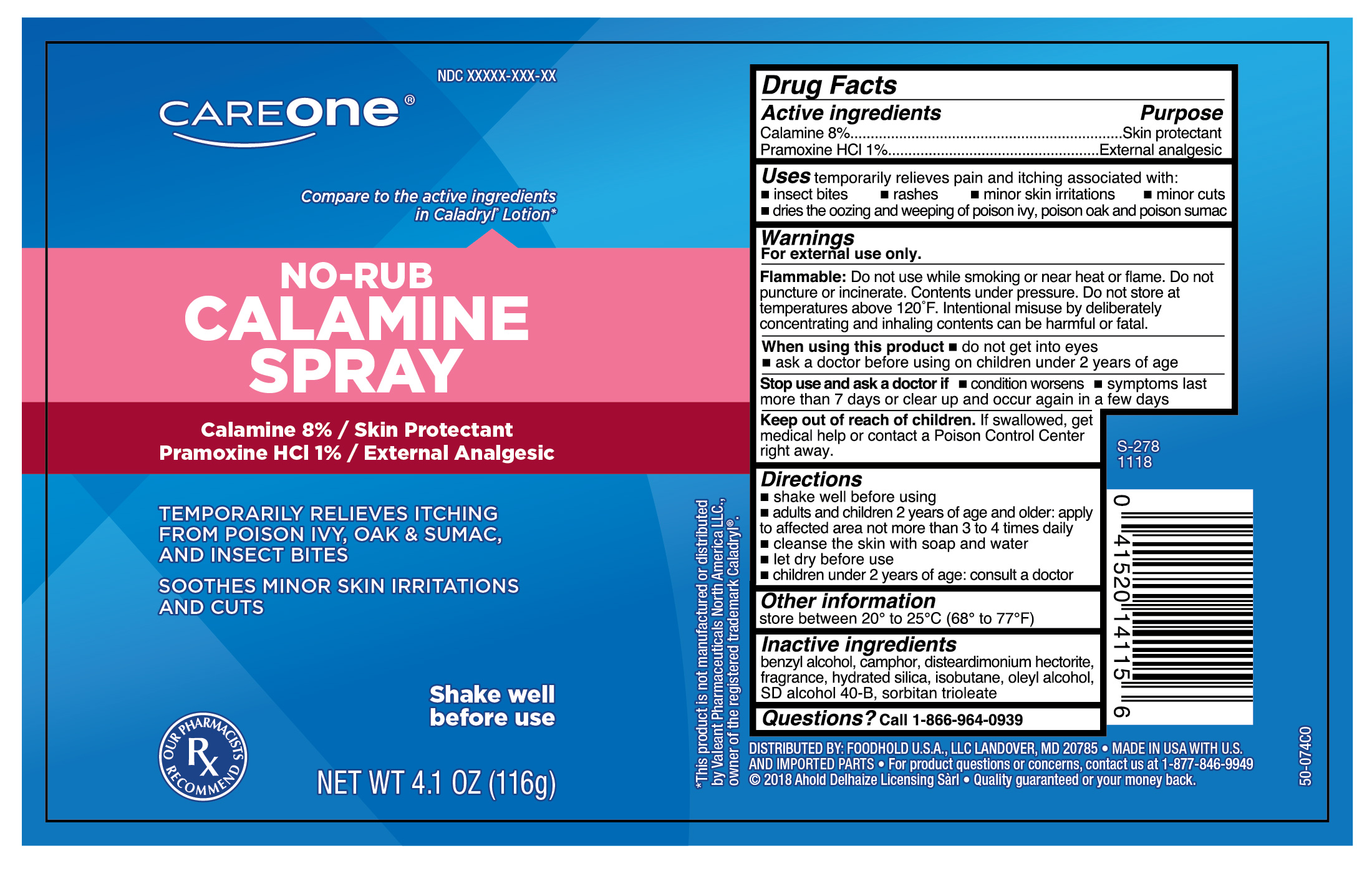 DRUG LABEL: Calamine Plus Pramoxine HCl
NDC: 41520-184 | Form: AEROSOL, SPRAY
Manufacturer: Foodhold USA
Category: otc | Type: HUMAN OTC DRUG LABEL
Date: 20241107

ACTIVE INGREDIENTS: ZINC OXIDE 24.16 mg/116 g; PRAMOXINE HYDROCHLORIDE 2.72 mg/116 g; FERRIC OXIDE RED 0.345 mg/116 g
INACTIVE INGREDIENTS: HYDRATED SILICA; OLEYL ALCOHOL; ALCOHOL; SORBITAN TRIOLEATE; DISTEARDIMONIUM HECTORITE; ISOBUTANE; BENZYL ALCOHOL; CAMPHOR (SYNTHETIC)

CareOne Calamine Plus Spray

Active Ingredient

Calamine 8%
Pramoxine HCl 1%

Purpose

Skin protectant
External analgesic

Uses

temporarily relieves pain and itching associated with:

- insect bites
- rashes
- minor skin irritations
- minor cuts
- dries the oozing and weeping of poison ivy, poison oak and poison sumac

Warnings

For external use only.

When using this product

- do not get into eyes
- ask a doctor before using on children under 2 years of age

Stop use and ask a doctor if

- conditions worsens
- symptoms last more than 7 days or clear up and occur again in a few days

Keep out of reach of children.

If swallowed, get medical help or contact a Poison Control Center right away.

Directions

- shake well before using
- adults and children 2 years of age and older: apply as needed to the affected area, not more than 3 or 4 times daily
- cleanse the skin with soap and water
- let dry before use
- children under 2 years of age: consult a doctor

Other information

store between 20° to 25°C (68° to 77°F)

Inactive ingredients

benzyl alcohol, camphor, disteardimonium hectorite, fragrance, hydrated silica, isobutane, oleyl alcohol, SD alcohol 40-B, sorbitan trioleate

Questions?

Call 1-866-964-0939

Principal Display Panel

CareOne

NO-RUB CALAMINE SPRAY

Calamine 8%/ Skin Protectant

Pramoxine HCl 1%/ External Analgesic

TEMPORARILY RELIEVES ITCHING FROM POISON IVY, OAK & SUMAC, AND INSECT BITES

SOOTHES MINOR SKIN IRRITATIONS AND CUTS

Shake well before use

NET WT 4.1 OZ (116g)